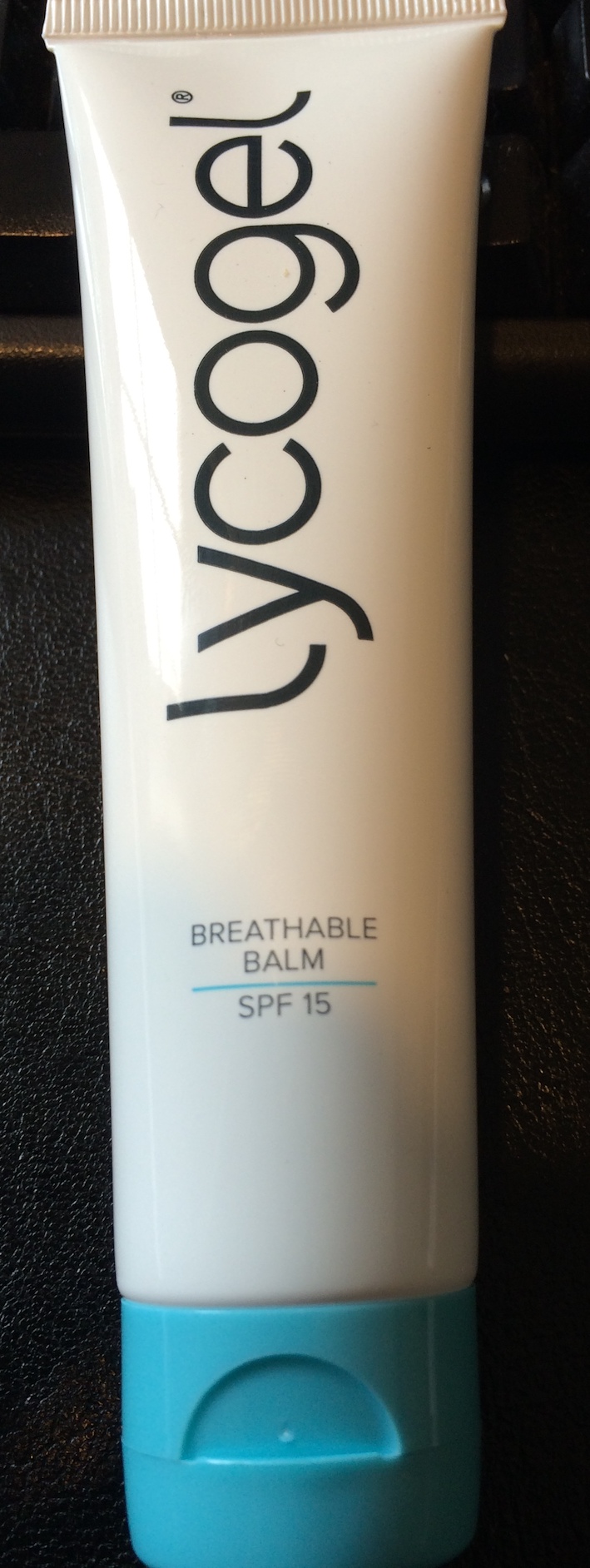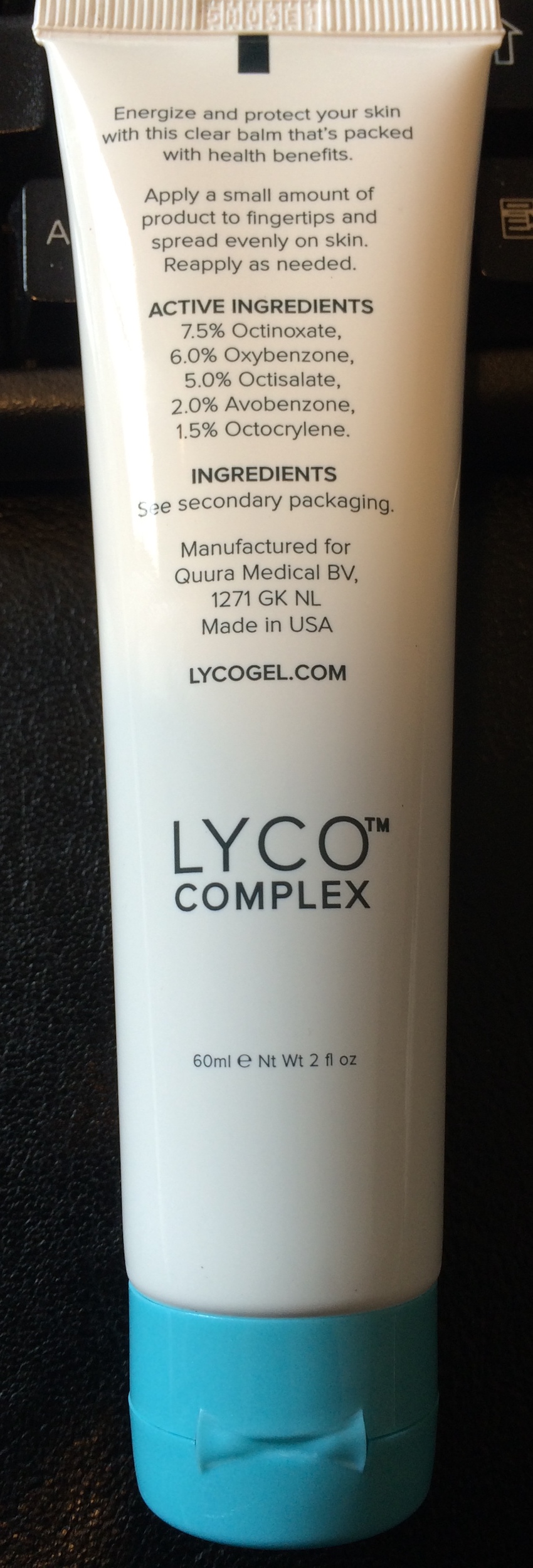 DRUG LABEL: Lycogel Breathable Balm
NDC: 51790-400 | Form: CREAM
Manufacturer: Quura Medical B.V
Category: otc | Type: HUMAN OTC DRUG LABEL
Date: 20180101

ACTIVE INGREDIENTS: OCTINOXATE 75 mg/1 mL; OXYBENZONE 60 mg/1 mL; OCTISALATE 50 mg/1 mL; AVOBENZONE 20 mg/1 mL; OCTOCRYLENE 15 mg/1 mL
INACTIVE INGREDIENTS: WATER; ALKYL (C12-15) BENZOATE; OCTYLDODECYL NEOPENTANOATE; MEDIUM-CHAIN TRIGLYCERIDES; GLYCERIN; HYALURONATE SODIUM; GREEN TEA LEAF; TEPRENONE; DIMETHICONE CROSSPOLYMER (450000 MPA.S AT 12% IN CYCLOPENTASILOXANE); CYCLOMETHICONE 4; KIWI FRUIT; CHLORELLA VULGARIS; ARTEMISIA VULGARIS WHOLE; SACCHAROMYCES LYSATE; CENTELLA ASIATICA; ECHINACEA PURPUREA; CARBOXYPOLYMETHYLENE; CARBOMER INTERPOLYMER TYPE A (ALLYL SUCROSE CROSSLINKED); POLYETHYLENE GLYCOL 400; TROLAMINE; PHENOXYETHANOL; CAPRYLYL GLYCOL; ETHYLHEXYLGLYCERIN; HEXYLENE GLYCOL; TOCOPHEROL; ASCORBYL PALMITATE; CITRIC ACID MONOHYDRATE; ZINC PIDOLATE; MANNITOL; LONICERA JAPONICA FLOWER; SODIUM CITRATE; XANTHIUM SIBIRICUM FRUIT; ALOE VERA LEAF; CYPERUS ROTUNDUS TUBER; ACETYL TETRAPEPTIDE-15; SODIUM BENZOATE; SORBITAN MONOOLEATE; POLYSORBATE 20; PALMITOYL PENTAPEPTIDE-4; ARCTOSTAPHYLOS UVA-URSI LEAF; OLEA EUROPAEA LEAF; DARUTOSIDE; XANTHAN GUM; ARABIDOPSIS THALIANA; UBIDECARENONE; IDEBENONE; EDETATE DISODIUM; OMEGA-3 FATTY ACIDS; VITAMIN A PALMITATE; .BETA.-CAROTENE; ASCORBIC ACID; APPLE; LECITHIN, SOYBEAN

Actives

OCTINOXATE,OXYBENZONE,OCTISALATE and AVOBENZONE

Inactives

Water (Aqua)

C12-15 Alkyl Benzoate

Octinoxate

Oxybenzone

Octisalate

Butylene Glycol

Octyldodecyl Neopentanoate

Caprylic/Capric Triglyceride

Avobenzone

Octocrylene

Glycerin

Sodium Hyaluronate

Camellia Sinensis Leaf Extract

Teprenone

Cyclopentasiloxane

Cyclohexasiloxane

Actinidia Chinensis (Kiwi) Fruit Extract

Algae Extract

Artemisia Vulgaris Extract

Saccharomyces Lysate Extract

Centella Asiatica Extract

Echinacea Purpurea Extract

Yeast Polysaccharides

Carbomer

Acrylates/C10-30 Alkyl Acrylate Crosspolymer

PEG-8

Triethanolamine

Phenoxyethanol

Caprylyl Glycol

Ethylhexylglycerin

Hexylene Glycol

Tocopherol

Ascorbyl Palmitate

Citric Acid

Zinc PCA

Mannitol

Lonicera Japonica (Honeysuckle) Flower Extract

Sodium Citrate

Xanthium Sibiricum Fruit Extract

Aloe Barbadensis Leaf Extract

Cyperus Rotundus Root Extract

Acetyl Tetrapeptide-15

Sodium Benzoate

Sorbitan Oleate

Polysorbate 20

Palmitoyl Pentapeptide-4

Arctostaphylos Uva Ursi Leaf Extract

Plankton Extract

Mitracarpus Scaber Extract

Olea Europaea (Olive) Leaf Extract

Darutoside

Xanthan Gum

Micrococcus Lysate

Arabidopsis Thaliana Extract

Ubiquinone

Hydroxydecyl Ubiquinone

Disodium EDTA

Phospholipids

Retinyl Palmitate

Beta-Carotene

Ascorbic Acid

Malus Domestica Fruit Cell Culture Extract

Lecithin